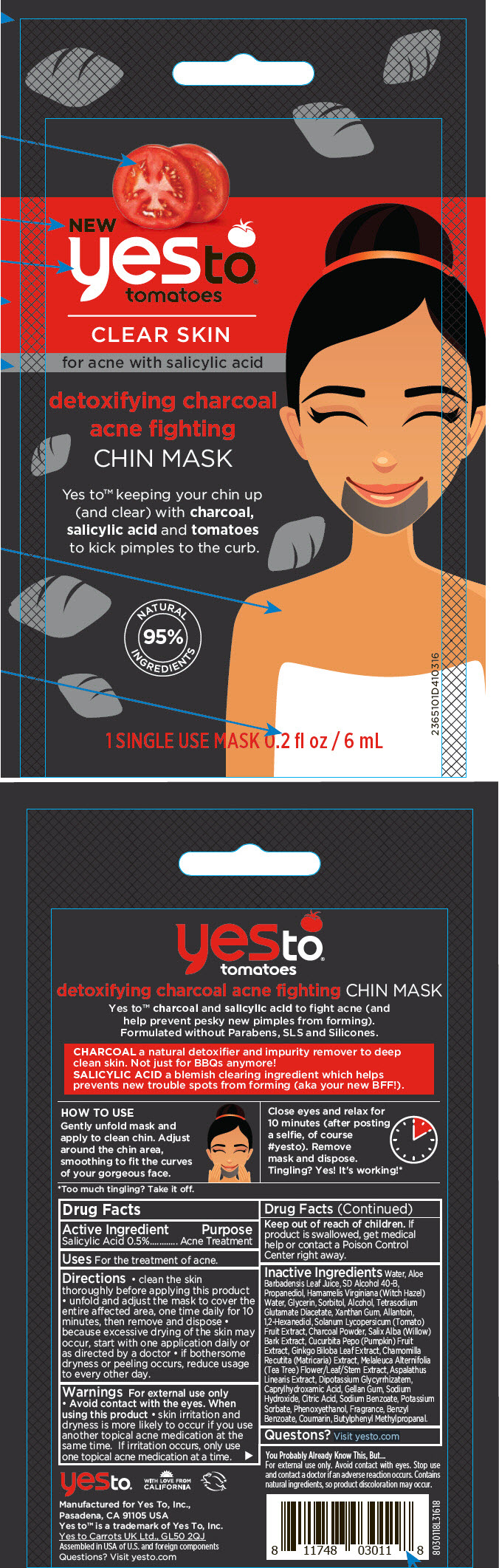 DRUG LABEL: Yes To Tomatoes Detoxifying Charcoal Acne Fighting Chin Mask
NDC: 69840-013 | Form: STRIP
Manufacturer: Yes To, Inc.
Category: otc | Type: HUMAN OTC DRUG LABEL
Date: 20190222

ACTIVE INGREDIENTS: SALICYLIC ACID 5 mg/1 mL
INACTIVE INGREDIENTS: ALOE VERA LEAF; WATER; HAMAMELIS VIRGINIANA TOP WATER; PROPANEDIOL; ALLANTOIN; GLYCERIN; ACTIVATED CHARCOAL; SOLANUM LYCOPERSICUM; MELALEUCA ALTERNIFOLIA LEAF; SORBITOL; TETRASODIUM GLUTAMATE DIACETATE; ENOXOLONE DIPOTASSIUM; XANTHAN GUM; CAPRYLHYDROXAMIC ACID; GELLAN GUM (LOW ACYL); SALIX ALBA BARK; GINKGO; PHENOXYETHANOL; PUMPKIN; MATRICARIA CHAMOMILLA LEAF; ASPALATHUS LINEARIS LEAF; CITRIC ACID MONOHYDRATE; SODIUM HYDROXIDE; 1,2-HEXANEDIOL; SODIUM BENZOATE; POTASSIUM SORBATE; ALCOHOL

Yes To™ Tomatoes Detoxifying Charcoal Acne Fighting Chin Mask

Drug Facts

Active Ingredient

Salicylic Acid 0.5%

Purpose

Acne Treatment

Uses

For the treatment of acne.

Directions

- clean the skin thoroughly before applying this product
- unfold and adjust the mask to cover the entire affected area, one time daily for 10 minutes, then remove and dispose
- because excessive drying of the skin may occur, start with one application daily or as directed by a doctor
- if bothersome dryness or peeling occurs, reduce usage to every other day.

Warnings

For external use only

- Avoid contact with the eyes.

When using this product

- skin irritation and dryness is more likely to occur if you use another topical acne medication at the same time. If irritation occurs, only use one topical acne medication at a time.

Keep out of reach of children. If product is swallowed, get medical help or contact a Poison Control Center right away.

Inactive Ingredients

Water, Aloe Barbadensis Leaf Juice, SD Alcohol 40-B, Propanediol, Hamamelis Virginiana (Witch Hazel) Water, Glycerin, Sorbitol, Alcohol, Tetrasodium Glutamate Diacetate, Xanthan Gum, Allantoin, 1,2-Hexanediol, Solanum Lycopersicum (Tomato) Fruit Extract, Charcoal Powder, Salix Alba (Willow) Bark Extract, Cucurbita Pepo (Pumpkin) Fruit Extract, Ginkgo Biloba Leaf Extract, Chamomilla Recutita (Matricaria) Extract, Melaleuca Alternifolia (Tea Tree) Flower/Leaf/Stem Extract, Aspalathus Linearis Extract, Dipotassium Glycyrrhizatem, Caprylhydroxamic Acid, Gellan Gum, Sodium Hydroxide, Citric Acid, Sodium Benzoate, Potassium Sorbate, Phenoxyethanol, Fragrance, Benzyl Benzoate, Coumarin, Butylphenyl Methylpropanal.

Questons?

Visit yesto.com

PRINCIPAL DISPLAY PANEL - 6 mL Mask Pouch

NEW
yesto®
tomatoes

CLEAR SKIN

for acne with salicylic acid

detoxifying charcoal
acne fighting

CHIN MASK

Yes to™ keeping your chin up
(and clear) with charcoal,
salicylic acid and tomatoes
to kick pimples to the curb.

NATURAL
95%
INGREDIENTS

1 SINGLE USE MASK 0.2 fl oz / 6 mL

2365101D410316